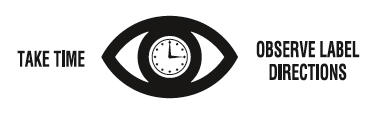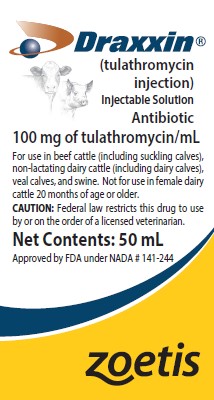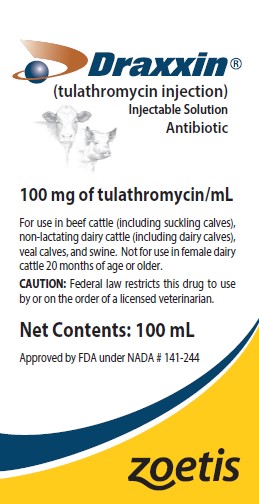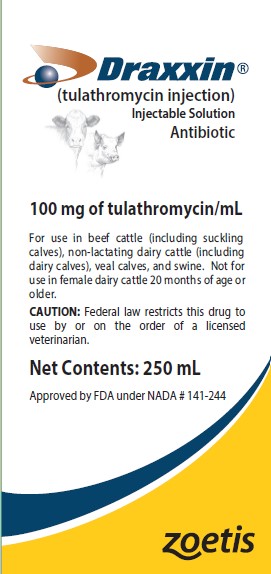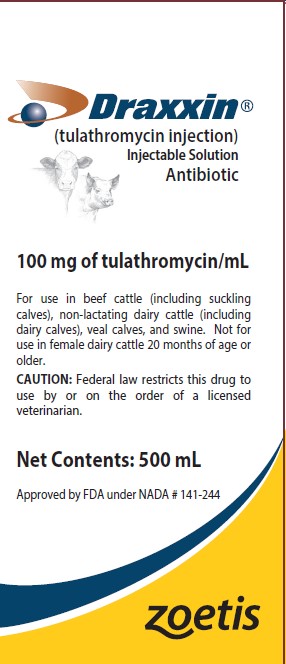 DRUG LABEL: Draxxin
NDC: 54771-8174 | Form: INJECTION, SOLUTION
Manufacturer: Zoetis Inc.
Category: animal | Type: PRESCRIPTION ANIMAL DRUG LABEL
Date: 20260127

ACTIVE INGREDIENTS: TULATHROMYCIN 100 mg/1 mL

Draxxin®
(tulathromycin injection)
Injectable Solution

Antibiotic

100 mg of tulathromycin/mL

For use in beef cattle (including suckling calves), non-lactating dairy cattle (including dairy calves), veal calves, and swine. Not for use in female dairy cattle 20 months of age or older.

CAUTION

Federal law restricts this drug to use by or on the order of a licensed veterinarian.

DESCRIPTION

DRAXXIN Injectable Solution is a ready-to-use sterile parenteral preparation containing tulathromycin, a semi-synthetic macrolide antibiotic of the subclass triamilide. Each mL of DRAXXIN contains 100 mg of tulathromycin, 500 mg propylene glycol, 19.2 mg citric acid and 5 mg monothioglycerol. Sodium hydroxide or hydrochloric acid may be added to adjust pH.
DRAXXIN consists of an equilibrated mixture of two isomeric forms of tulathromycin in a 9:1 ratio.

INDICATIONS

Beef and Non-Lactating Dairy Cattle

BRD – DRAXXIN Injectable Solution is indicated for the treatment of bovine respiratory disease (BRD) associated with Mannheimia haemolytica, Pasteurella multocida, Histophilus somni, and Mycoplasma bovis; and for the control of respiratory disease in cattle at high risk of developing BRD associated with Mannheimia haemolytica, Pasteurella multocida, Histophilus somni, and Mycoplasma bovis.

IBK – DRAXXIN Injectable Solution is indicated for the treatment of infectious bovine keratoconjunctivitis (IBK) associated with Moraxella bovis.

Foot Rot – DRAXXIN Injectable Solution is indicated for the treatment of bovine foot rot (interdigital necrobacillosis) associated with Fusobacterium necrophorum and Porphyromonas levii.

Suckling Calves, Dairy Calves, and Veal Calves

BRD – DRAXXIN Injectable Solution is indicated for the treatment of BRD associated with M. haemolytica, P. multocida, H. somni, and M. bovis.

Swine

DRAXXIN Injectable Solution is indicated for the treatment of swine respiratory disease (SRD) associated with Actinobacillus pleuropneumoniae, Pasteurella multocida, Bordetella bronchiseptica, Haemophilus parasuis, and Mycoplasma hyopneumoniae; and for the control of SRD associated with Actinobacillus pleuropneumoniae, Pasteurella multocida, and Mycoplasma hyopneumoniae in groups of pigs where SRD has been diagnosed.

DOSAGE AND ADMINISTRATION

Cattle

Inject subcutaneously as a single dose in the neck at a dosage of 2.5 mg/kg (1.1 mL/100 lb) body weight (BW). Do not inject more than 10 mL per injection site.

Table 1. DRAXXIN Cattle Dosing Guide
Animal Weight (Pounds) | Dose Volume (mL)
100 | 1.1
200 | 2.3
300 | 3.4
400 | 4.5
500 | 5.7
600 | 6.8
700 | 8.0
800 | 9.1
900 | 10.2
1000 | 11.4

Swine

Inject intramuscularly as a single dose in the neck at a dosage of 2.5 mg/kg (0.25 mL/22 lb) BW. Do not inject more than 2.5 mL per injection site.

Table 2. DRAXXIN Swine Dosing Guide
Animal Weight (Pounds) | Dose Volume (mL)
15 | 0.2
30 | 0.3
50 | 0.6
70 | 0.8
90 | 1.0
110 | 1.3
130 | 1.5
150 | 1.7
170 | 1.9
190 | 2.2
210 | 2.4
230 | 2.6
250 | 2.8
270 | 3.1
290 | 3.3

CONTRAINDICATIONS

The use of DRAXXIN Injectable Solution is contraindicated in animals previously found to be hypersensitive to the drug.

WARNINGS

FOR USE IN ANIMALS ONLY.

NOT FOR HUMAN USE.

KEEP OUT OF REACH OF CHILDREN.

NOT FOR USE IN CHICKENS OR TURKEYS.

RESIDUE WARNINGS

Cattle

Cattle intended for human consumption must not be slaughtered within 18 days from the last treatment. Do not use in female dairy cattle 20 months of age or older.

Swine

Swine intended for human consumption must not be slaughtered within 5 days from the last treatment.

PRECAUTIONS

Cattle

The effects of DRAXXIN on bovine reproductive performance, pregnancy, and lactation have not been determined. Subcutaneous injection can cause a transient local tissue reaction that may result in trim loss of edible tissue at slaughter.

Swine

The effects of DRAXXIN on porcine reproductive performance, pregnancy, and lactation have not been determined. Intramuscular injection can cause a transient local tissue reaction that may result in trim loss of edible tissue at slaughter.

ADVERSE REACTIONS

Cattle

In one BRD field study, two calves treated with DRAXXIN at 2.5 mg/kg BW exhibited transient hypersalivation. One of these calves also exhibited transient dyspnea, which may have been related to pneumonia.

Swine

In one field study, one out of 40 pigs treated with DRAXXIN at 2.5 mg/kg BW exhibited mild salivation that resolved in less than four hours.

POST APPROVAL EXPERIENCE

The following adverse events are based on post approval adverse drug experience reporting. Not all adverse events are reported to the FDA CVM. It is not always possible to reliably estimate the adverse event frequency or establish a causal relationship to product exposure using these data. The following adverse events are listed in decreasing order of reporting frequency in cattle: Injection site reactions and anaphylaxis/anaphylactoid reactions. For a complete listing of adverse reactions for DRAXXIN (tulathromycin injection) Injectable Solution reported to the CVM see: http://www.fda.gov/AnimalVeterinary.

CLINICAL PHARMACOLOGY

At physiological pH, tulathromycin (a weak base) is approximately 50 times more soluble in hydrophilic than hydrophobic media. This solubility profile is consistent with the extracellular pathogen activity typically associated with the macrolides. [Carbon, C. 1998. Pharmacodynamics of Macrolides, Azalides, and Streptogramins: Effect on Extracellular Pathogens. Clin. Infect. Dis., 27:28-32.] Markedly higher tulathromycin concentrations are observed in the lungs as compared to the plasma. The extent to which lung concentrations represent free (active) drug was not examined. Therefore, the clinical relevance of these elevated lung concentrations is undetermined.

Although the relationship between tulathromycin and the characteristics of its antimicrobial effects has not been characterized, as a class, macrolides tend to be primarily bacteriostatic, but may be bactericidal against some pathogens. [Nightingale, C.J. 1997. Pharmacokinetics and Pharmacodynamics of Newer Macrolides. Pediatr. Infect. Dis. J., 16:438-443.] They also tend to exhibit concentration independent killing; the rate of bacterial eradication does not change once serum drug concentrations reach 2 to 3 times the minimum inhibitory concentration (MIC) of the targeted pathogen. Under these conditions, the time that serum concentrations remain above the MIC becomes the major determinant of antimicrobial activity. Macrolides also exhibit a post-antibiotic effect (PAE), the duration of which tends to be both drug and pathogen dependent. In general, by increasing the macrolide concentration and the exposure time, the PAE will increase to some maximal duration. Of the two variables, concentration and exposure time, drug concentration tends to be the most powerful determinant of the duration of PAE.

Tulathromycin is eliminated from the body primarily unchanged via biliary excretion.

^1 Carbon, C. 1998. Pharmacodynamics of Macrolides, Azalides, and Streptogramins: Effect on Extracellular Pathogens. Clin. Infect. Dis., 27:28-32.
^2 Nightingale, C.J. 1997. Pharmacokinetics and Pharmacodynamics of Newer Macrolides. Pediatr. Infect. Dis. J., 16:438-443.

Cattle

Following subcutaneous administration into the neck of feeder calves at a dosage of 2.5 mg/kg BW, tulathromycin is rapidly and nearly completely absorbed. Peak plasma concentrations generally occur within 15 minutes after dosing and product relative bioavailability exceeds 90%. Total systemic clearance is approximately 170 mL/hr/kg. Tulathromycin distributes extensively into body tissues, as evidenced by volume of distribution values of approximately 11 L/kg in healthy ruminating calves. [Clearance and volume estimates are based on intersubject comparisons of 2.5 mg/kg BW administered by either subcutaneous or intravenous injection.] This extensive volume of distribution is largely responsible for the long elimination half-life of this compound [approximately 2.75 days in the plasma (based on quantifiable terminal plasma drug concentrations) versus 8.75 days for total lung concentrations (based on data from healthy animals)]. Linear pharmacokinetics are observed with subcutaneous doses ranging from 1.27 mg/kg BW to 5.0 mg/kg BW. No pharmacokinetic differences are observed in castrated male versus female calves.

^3 Clearance and volume estimates are based on intersubject comparisons of 2.5 mg/kg BW administered by either subcutaneous or intravenous injection.

Swine

Following intramuscular administration to feeder pigs at a dosage of 2.5 mg/kg BW, tulathromycin is completely and rapidly absorbed (Tmax ~0.25 hour). Subsequently, the drug rapidly distributes into body tissues, achieving a volume of distribution exceeding 15 L/kg. The free drug is rapidly cleared from the systemic circulation (CLsystemic = 187 mL/hr/kg). However, it has a long terminal elimination half-life (60 to 90 hours) owing to its extensive volume of distribution. Although pulmonary tulathromycin concentrations are substantially higher than concentrations observed in the plasma, the clinical significance of these findings is undetermined. There are no gender differences in swine tulathromycin pharmacokinetics.

MICROBIOLOGY

Cattle

Tulathromycin has demonstrated in vitro activity against Mannheimia haemolytica, Pasteurella multocida, Histophilus somni, and Mycoplasma bovis, four pathogens associated with BRD; against Moraxella bovis associated with IBK; and against Fusobacterium necrophorum and Porphyromonas levii associated with bovine foot rot.

The MICs of tulathromycin against indicated BRD and IBK pathogens were determined using methods recommended by the Clinical and Laboratory Standards Institute (CLSI, M31-A2). The MICs against foot rot pathogens were also determined using methods recommended by the CLSI (M11-A6). All MIC values were determined using the 9:1 isomer ratio of this compound.

BRD - The MICs of tulathromycin were determined for BRD isolates obtained from calves enrolled in therapeutic and at-risk field studies in the U.S. in 1999. In the therapeutic studies, isolates were obtained from pre-treatment nasopharyngeal swabs from all study calves, and from lung swabs or lung tissue of saline-treated calves that died. In the at-risk studies, isolates were obtained from nasopharyngeal swabs of saline-treated non-responders, and from lung swabs or lung tissue of saline-treated calves that died. The results are shown in Table 3.

IBK - The MICs of tulathromycin were determined for Moraxella bovis isolates obtained from calves enrolled in IBK field studies in the U.S. in 2004. Isolates were obtained from pre-treatment conjunctival swabs of calves with clinical signs of IBK enrolled in the DRAXXIN and saline-treated groups. The results are shown in Table 3.

Foot Rot - The MICs of tulathromycin were determined for Fusobacterium necrophorum and Porphyromonas levii obtained from cattle enrolled in foot rot field studies in the U.S. and Canada in 2007. Isolates were obtained from pretreatment interdigital biopsies and swabs of cattle with clinical signs of foot rot enrolled in the DRAXXIN and saline-treated groups. The results are shown in Table 3.

Table 3. Tulathromycin minimum inhibitory concentration (MIC) values [The correlation between in vitro susceptibility data and clinical effectiveness is unknown.] for indicated pathogens isolated from field studies evaluating BRD and IBK in the U.S. and from foot rot field studies in the U.S. and Canada.
Indicated pathogen | Date isolated | No. of isolates | MIC50 [The lowest MIC to encompass 50% and 90% of the most susceptible isolates, respectively.] (μg/mL) | MIC90 (μg/mL) | MIC range (μg/mL)
Mannheimia haemolytica | 1999 | 642 | 2 | 2 | 0.5 to 64
Pasteurella multocida | 1999 | 221 | 0.5 | 1 | 0.25 to 64
Histophilus somni | 1999 | 36 | 4 | 4 | 1 to 4
Mycoplasma bovis | 1999 | 43 | 0.125 | 1 | ≤ 0.063 to > 64
Moraxella bovis | 2004 | 55 | 0.5 | 0.5 | 0.25 to 1
Fusobacterium necrophorum | 2007 | 116 | 2 | 64 | ≤ 0.25 to > 128
Porphyromonas levii | 2007 | 103 | 8 | 128 | ≤ 0.25 to > 128

* The correlation between in vitro susceptibility data and clinical effectiveness is unknown.
**The lowest MIC to encompass 50% and 90% of the most susceptible isolates, respectively.

Swine

In vitro activity of tulathromycin has been demonstrated against Actinobacillus pleuropneumoniae, Pasteurella multocida, Bordetella bronchiseptica, Haemophilus parasuis, and Mycoplasma hyopneumoniae.

The MICs of tulathromycin against indicated SRD pathogens were determined using methods recommended by the Clinical and Laboratory Standards Institute (CLSI, M31-A and M31-A3). MICs for Haemophilus parasuis were determined using Veterinary Fastidious Medium and were incubated up to 48 hours at 35 to 37°C in a CO2-enriched atmosphere. All MIC values were determined using the 9:1 isomer ratio of this compound. Isolates obtained in 2000 and 2002 were from lung samples from saline-treated pigs and non-treated sentinel pigs enrolled in Treatment of SRD field studies in the U.S. and Canada. Isolates obtained in 2007 and 2008 were from lung samples from saline-treated and DRAXXIN-treated pigs enrolled in the Control of SRD field study in the U.S. and Canada. The results are shown in Table 4.

Table 4. Tulathromycin minimum inhibitory concentration (MIC) values [The correlation between in vitro susceptibility data and clinical effectiveness is unknown.] for indicated pathogens isolated from field studies evaluating SRD in the U.S. and Canada.
Indicated pathogen | Date isolated | No. of isolates | MIC50 [The lowest MIC to encompass 50% and 90% of the most susceptible isolates, respectively.] (μg/mL) | MIC90 (μg/mL) | MIC range (μg/mL)
Actinobacillus pleuropneumoniae | 2000-2002 2007-2008 | 135 88 | 16 16 | 32 16 | 16 to 32 4 to 32
Haemophilus parasuis | 2000-2002 | 31 | 1 | 2 | 0.25 to > 64
Pasteurella multocida | 2000-2002 2007-2008 | 55 40 | 1 1 | 2 2 | 0.5 to > 64 ≤ 0.03 to 2
Bordetella bronchiseptica | 2000-2002 | 42 | 4 | 8 | 2 to 8

* The correlation between in vitro susceptibility data and clinical effectiveness is unknown.

** The lowest MIC to encompass 50% and 90% of the most susceptible isolates, respectively.

EFFECTIVENESS

Cattle

BRD – In a multi-location field study, 314 calves with naturally occurring BRD were treated with DRAXXIN. Responses to treatment were compared to saline-treated controls. A cure was defined as a calf with normal attitude/activity, normal respiration, and a rectal temperature of ≤ 104°F on Day 14. The cure rate was significantly higher (P ≤ 0.05) in DRAXXIN-treated calves (78%) compared to saline-treated calves (24%). There were two BRD-related deaths in the DRAXXIN-treated calves compared to nine BRD-related deaths in the saline-treated calves.

Fifty-two DRAXXIN-treated calves and 27 saline-treated calves from the multi-location field BRD treatment study had Mycoplasma bovis identified in cultures from pre-treatment nasopharyngeal swabs. Of the 52 DRAXXIN-treated calves, 37 (71.2%) calves were categorized as cures and 15 (28.8%) calves were categorized as treatment failures. Of the 27 saline-treated calves, 4 (14.8%) calves were categorized as cures and 23 (85.2%) calves were treatment failures.

A Bayesian meta-analysis was conducted to compare the BRD treatment success rate in young calves (calves weighing 250 lbs or less and fed primarily a milk-based diet) treated with DRAXXIN to the success rate in older calves (calves weighing more than 250 lbs and fed primarily a roughage and grain-based diet) treated with DRAXXIN. The analysis included data from four BRD treatment effectiveness studies conducted for the approval of DRAXXIN in the U.S. and nine contemporaneous studies conducted in Europe. The analysis showed that the BRD treatment success rate in young calves was at least as good as the BRD treatment success rate in older calves. As a result, DRAXXIN is considered effective for the treatment of BRD associated with M. haemolytica, P. multocida, H. somni, and M. bovis in suckling calves, dairy calves, and veal calves.

In another multi-location field study with 399 calves at high risk of developing BRD, administration of DRAXXIN resulted in a significantly reduced incidence of BRD (11%) compared to saline-treated calves (59%). Effectiveness evaluation was based on scored clinical signs of normal attitude/ activity, normal respiration, and a rectal temperature of ≤ 104°F on Day 14. There were no BRD-related deaths in the DRAXXIN-treated calves compared to two BRD-related deaths in the saline-treated calves. Fifty saline-treated calves classified as non-responders in this study had Mycoplasma bovis identified in cultures of post-treatment nasopharyngeal swabs or lung tissue.

Two induced infection model studies were conducted to confirm the effectiveness of DRAXXIN against Mycoplasma bovis. A total of 166 calves were inoculated intratracheally with field strains of Mycoplasma bovis. When calves became pyrexic and had abnormal respiration scores, they were treated with either DRAXXIN (2.5 mg/kg BW) subcutaneously or an equivalent volume of saline. Calves were observed for signs of BRD for 14 days post-treatment, then were euthanized and necropsied. In both studies, mean lung lesion percentages were statistically significantly lower in the DRAXXIN-treated calves compared with saline-treated calves (11.3% vs. 28.9%, P = 0.0001 and 15.0% vs. 30.7%, P < 0.0001).

IBK – Two field studies were conducted evaluating DRAXXIN for the treatment of IBK associated with Moraxella bovis in 200 naturally-infected calves. The primary clinical endpoint of these studies was cure rate, defined as a calf with no clinical signs of IBK and no corneal ulcer, assessed on Days 5, 9, 13, 17, and 21. Time to improvement, defined as the first day on which a calf had no clinical signs of IBK in both eyes, provided that those scores were maintained at the next day of observation, was assessed as a secondary variable. At all time points, in both studies, the cure rate was significantly higher (P < 0.05) for DRAXXIN-treated calves compared to saline-treated calves. Additionally, time to improvement was significantly less (P < 0.0001) in both studies for DRAXXIN-treated calves compared to saline-treated calves.

Foot Rot - The effectiveness of DRAXXIN for the treatment of bovine foot rot was evaluated in 170 cattle in two field studies. Cattle diagnosed with bovine foot rot were enrolled and treated with a single subcutaneous dose of DRAXXIN (2.5 mg/kg BW) or an equivalent volume of saline. Cattle were clinically evaluated 7 days after treatment for treatment success, which was based on defined decreases in lesion, swelling, and lameness scores. In both studies, the treatment success percentage was statistically significantly higher in DRAXXIN-treated calves compared with saline-treated calves (60% vs. 8%, P < 0.0001 and 83.3% vs. 50%, P = 0.0088).

Swine

In a multi-location field study to evaluate the treatment of naturally occurring SRD, 266 pigs were treated with DRAXXIN. Responses to treatment were compared to saline-treated controls. Success was defined as a pig with normal attitude, normal respiration, and rectal temperature of < 104°F on Day 7. The treatment success rate was significantly greater (P ≤ 0.05) in DRAXXIN-treated pigs (70.5%) compared to saline-treated pigs (46.1%). M. hyopneumoniae was isolated from 106 saline-treated and non-treated sentinel pigs in this study.

Two induced infection model studies were conducted to confirm the effectiveness of DRAXXIN against M. hyopneumoniae. Ten days after inoculation intranasally and intratracheally with a field strain of M. hyopneumoniae, 144 pigs were treated with either DRAXXIN (2.5 mg/kg BW) intramuscularly or an equivalent volume of saline. Pigs were euthanized and necropsied 10 days post-treatment. The mean percentage of gross pneumonic lung lesions was statistically significantly lower (P < 0.0001) for DRAXXIN-treated pigs than for saline-treated pigs in both studies (8.52% vs. 23.62% and 11.31% vs. 26.42%).

The effectiveness of DRAXXIN for the control of SRD was evaluated in a multi-location natural infection field study. When at least 15% of the study candidates showed clinical signs of SRD, all pigs were enrolled and treated with DRAXXIN (226 pigs) or saline (227 pigs). Responses to treatment were evaluated on Day 7. Success was defined as a pig with normal attitude, normal respiration, and rectal temperature of < 104°F. The treatment success rate was significantly greater (P < 0.05) in DRAXXIN-treated pigs compared to saline-treated pigs (59.2% vs. 41.2%).

ANIMAL SAFETY

Cattle

Safety studies were conducted in feeder calves receiving a single subcutaneous dose of 25 mg/kg BW, or 3 weekly subcutaneous doses of 2.5, 7.5, or 12.5 mg/kg BW. In all groups, transient indications of pain after injection were seen, including head shaking and pawing at the ground. Injection site swelling, discoloration of the subcutaneous tissues at the injection site and corresponding histopathologic changes were seen in animals in all dosage groups. These lesions showed signs of resolving over time. No other drug-related lesions were observed macroscopically or microscopically.

An exploratory study was conducted in feeder calves receiving a single subcutaneous dose of 10, 12.5, or 15 mg/kg BW. Macroscopically, no lesions were observed. Microscopically, minimal to mild myocardial degeneration was seen in one of six calves administered 12.5 mg/kg BW and two of six calves administered 15 mg/kg BW.

A safety study was conducted in preruminant calves 13 to 27 days of age receiving 2.5 mg/kg BW or 7.5 mg/kg BW once subcutaneously. With the exception of minimal to mild injection site reactions, no drug-related clinical signs or other lesions were observed macroscopically or microscopically.

Swine

Safety studies were conducted in pigs receiving a single intramuscular dose of 25 mg/kg BW, or 3 weekly intramuscular doses of 2.5, 7.5, or 12.5 mg/kg BW. In all groups, transient indications of pain after injection were seen, including restlessness and excessive vocalization. Tremors occurred briefly in one animal receiving 7.5 mg/kg BW. Discoloration and edema of injection site tissues and corresponding histopathologic changes were seen in animals at all dosages and resolved over time. No other drug-related lesions were observed macroscopically or microscopically.

STORAGE CONDITIONS

Store below 25°C (77°F), with excursions up to 40°C (104°F). Use this product within 45 days of the first puncture and puncture a maximum of 20 times. If more than 20 punctures are anticipated, the use of automatic injection equipment of a repeater syringe is recommended. When using a draw-off spike or needle with bore diameter larger than 16 gauge, discard any product remaining in the vial immediately after use.

HOW SUPPLIED

DRAXXIN Injectable Solution is available in the following package sizes:
50 mL vial
100 mL vial
250 mL vial
500 mL vial

Approved by FDA under NADA # 141-244
zoetis
Distributed by:
Zoetis Inc.
Kalamazoo, MI 49007

CONTACT INFORMATION

To report a suspected adverse reaction or to request a safety data sheet call 1-888-963-8471. For additional information about adverse drug experience reporting for animal drugs, contact FDA at 1-888-FDA-VETS or online at www.fda.gov/reportanimalae.
For additional DRAXXIN product information call: 1-888-DRAXXIN or go to www.zoetisus.com/products/cattle/draxxin

Revised: March 2025

PRINCIPAL DISPLAY PANEL - 50ml Box

50ml Box

40036994

PRINCIPAL DISPLAY PANEL - 100ml Box

100 mL Box

40037000

PRINCIPAL DISPLAY PANEL - 250ml Box

250ml Box

40036998

PRINCIPAL DISPLAY PANEL - 500ml Box

500ml Box
40036996